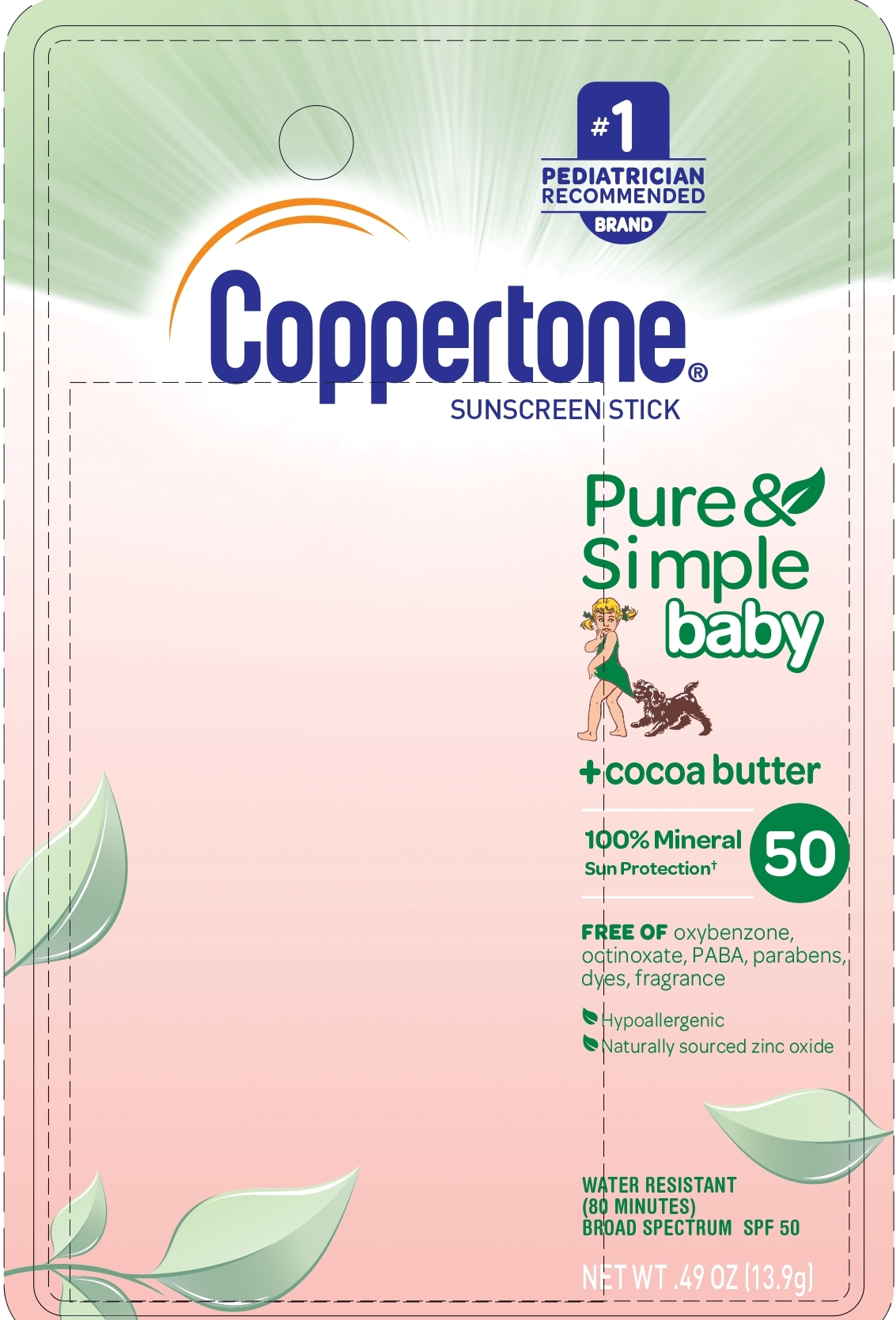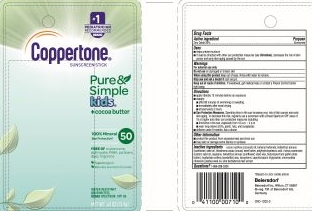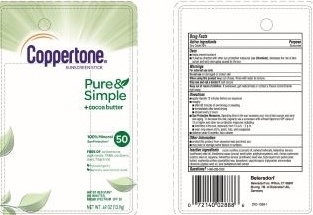 DRUG LABEL: Coppertone Sunscreen SPF 50
NDC: 66800-4115 | Form: STICK
Manufacturer: Beiersdorf Inc
Category: otc | Type: HUMAN OTC DRUG LABEL
Date: 20251231

ACTIVE INGREDIENTS: ZINC OXIDE 20 g/100 g
INACTIVE INGREDIENTS: COCONUT OIL; BEHENYL BEHENATE; COCOA BUTTER; RICINUS COMMUNIS SEED; SUNFLOWER SEED; CANDELILLA WAX; POLYHYDROXYSTEARIC ACID (2300 MW); SQUALANE; SHEA BUTTER; JOJOBA OIL; CAPRYLIC/CAPRIC/LAURIC TRIGLYCERIDE; TOCOPHEROL; ALOE VERA LEAF

Pure & Simple SPF 50 Sunscreen Stick

Active ingredient

Zinc Oxide 20%

Purpose

Sunscreen

Uses

■ helps prevent sunburn

■ if used as directed with other sun protection measures (see Directions), decreases the risk of skin cancer and early skin aging caused by the sun

Warnings

For external use only

Do not useon damaged or broken skin

WHEN USING

When using this productkeep out of eyes. Rinse with water to remove.

Stop use and ask a doctor ifrash occurs

Keep out of reach of children.If product is swallowed, get medical help or contact a Poison Control Center right away.

Directions

■ apply liberally 15 minutes before sun exposure

■ reapply:

■ after 80 minutes of swimming or sweating

■ immediately after towel drying

■ at least every 2 hours

■ Sun Protection Measures.Spending time in the sun increases your risk of skin cancer and early skin aging. To decrease this risk, regularly use a sunscreen with a Broad Spectrum SPF value of 15 or higher and other sun protection measures including:

■ limit time in the sun, especially from 10 a.m. – 2 p.m.

■ wear long-sleeve shirts, pants, hats, and sunglasses

■ children under 6 months: Ask a doctor

Other information

■ protect this product from excessive heat and direct sun

■ may stain or damage some fabrics or surfaces

Inactive ingredients

cocos nucifera (coconut) oil, behenyl behenate, helianthus annuus (sunflower) seed oil, theobroma cacao (cocoa) seed butter, polyhydroxystearic acid, ricinus communis (castor) seed oil, squalane, helianthus annuus (sunflower) seed wax, butyrospermum parkii (shea butter), euphorbia cerifera (candelilla) wax, tocopherol, caprylic/capric triglyceride, simmondsia chinensis (jojoba) seed oil, aloe barbadensis leaf extract

Questions?

1-866-288-3330

PACKAGE LABEL

Pure&Simple + cocoa butter

100% Minerla Sun Protection 50

Free of oxybenzone, octinoxate, PABA, dyes, fragrance

Hypoallergenic

Naturally sourced zinc oxide

Water Resistant (80 Minutes)

Broad Spectrum SPF 50

NET WT .49 OZ (13.9 g)